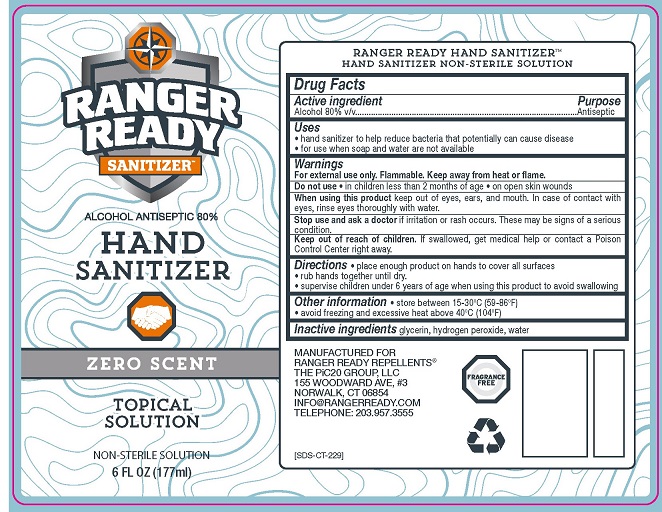 DRUG LABEL: Ranger Ready Hand Sanitizer
NDC: 74042-001 | Form: LIQUID
Manufacturer: The PiC20 Group, LLC dba Ranger Ready Repellents
Category: otc | Type: HUMAN OTC DRUG LABEL
Date: 20200421

ACTIVE INGREDIENTS: ALCOHOL 80 mL/100 mL
INACTIVE INGREDIENTS: GLYCERIN; HYDROGEN PEROXIDE; WATER

Ranger Ready Hand Sanitizer (Alcohol)

RANGER READY HAND SANITIZER™
HAND SANITIZER NON-STERILE SOLUTION
Drug Facts

Active ingredient

Alcohol 80% v/v

Purpose
Antiseptic

Uses

- hand sanitizer to help reduce bacteria that potentially can cause diseases
- for use when soap and water are not available

Warnings
For external use only
Flammable. Keep away from heat or flame

Do not use

- in children less than 2 months of age
- on open skin wounds

When using this product keep out of eyes, ears and mouth. In case of contact with eyes, rinse eyes thoroughly with water.

Stop use and ask a doctor if irritation or rash occurs. These may be signs of a serious condition.

Keep out of reach of children. If swallowed, get medical help or contact a Poison Control Center right away.

Directions

- place enough product on hands to cover all surfaces
- rub hands together until dry
- supervise children under 6 years of age when using this product to avoid swallowing

Other information

- store between 15-30°C (59-86°F)
- avoid freezing and excessive heat above 40°C (104°F)

Inactive ingredients glycerin, hydrogen peroxide, water

MANUFACTURED FOR

RANGER READY REPELLENTS®

THE PiC20 GROUP, LLC

155 WOODWARD AVE, #3

NORWALK, CT 06854

INFO@RANGERREADY.COM

TELEPHONE: 203.957.3555

PACKAGE LABEL

RANGER READY SANITIZER™

ALCOHOL ANTISEPTIC 80%

HAND SANITIZER

ZERO SCENT

TOPICAL SOLUTION

NON-STERILE SOLUTION

6 FL OZ (177 ml)